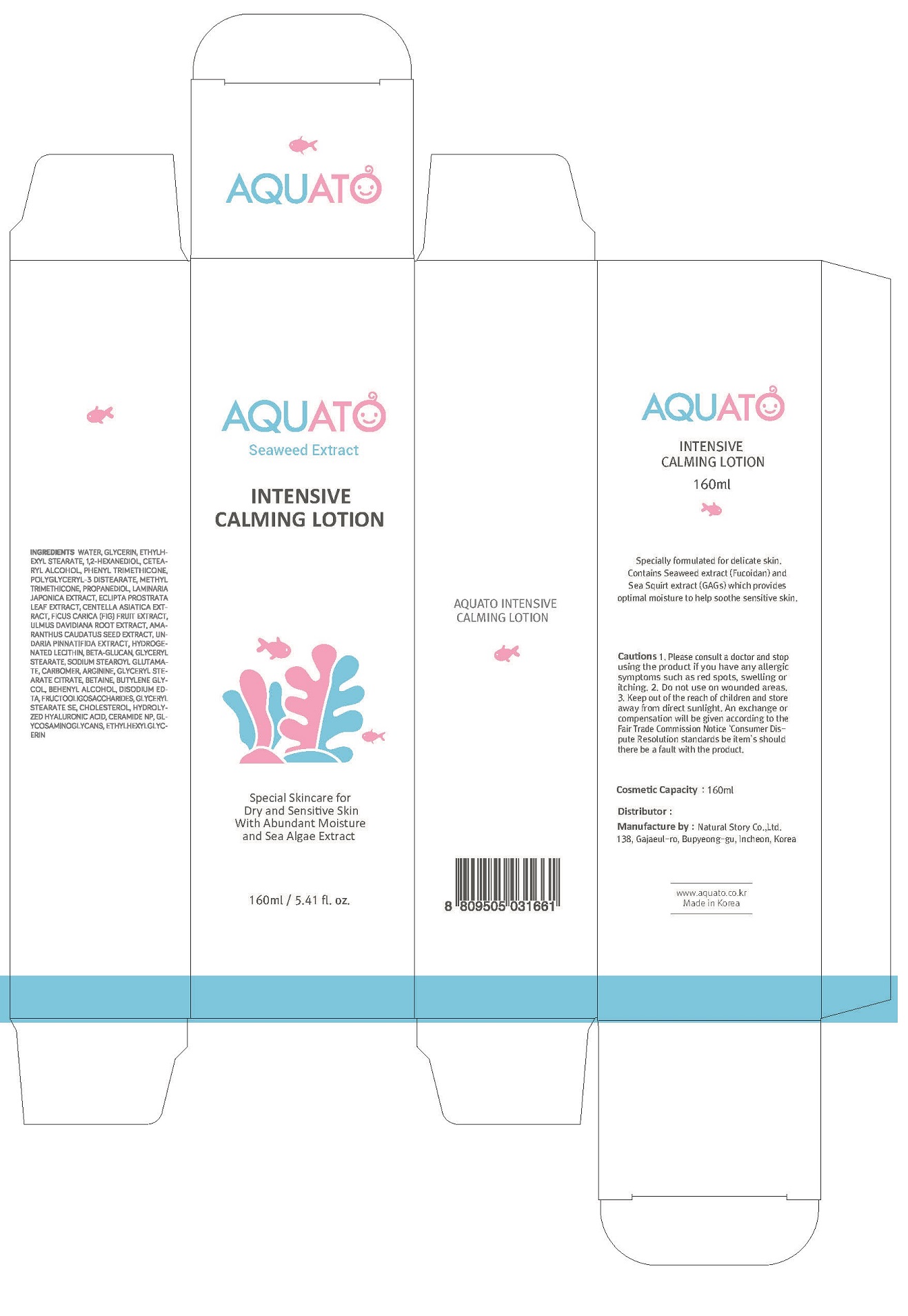 DRUG LABEL: Aquato Intensive CalmingLotion
NDC: 80972-0002 | Form: LOTION
Manufacturer: Natural Story Co.,Ltd.
Category: otc | Type: HUMAN OTC DRUG LABEL
Date: 20201225

ACTIVE INGREDIENTS: UNDARIA PINNATIFIDA 0.0005 g/100 mL; HYDROLYZED GLYCOSAMINOGLYCANS (BOVINE; 50000 MW) 0.001 g/100 mL
INACTIVE INGREDIENTS: WATER

Drug Facts

ACTIVE INGREDIENT

adenosne

INACTIVE INGREDIENT

WATER
GLYCERIN
ETHYLHEXYL STEARATE
1,2-HEXANEDIOL
CETEARYL ALCOHOL
POLYGLYCERYL-3 DISTEARATE
GLYCERYL STEARATE CITRATE
PHENYL TRIMETHICONE
WATER
DIPROPYLENE GLYCOL
GLYCERIN
LAMINARIA JAPONICA EXTRACT
ECLIPTA PROSTRATA LEAF EXTRACT
1,2-HEXANEDIOL
FRUCTOOLIGOSACCHARIDES
BETA-GLUCAN
HYDROGENATED LECITHIN
HYDROLYZED HYALURONIC ACID
METHYL TRIMETHICONE
PROPANEDIOL
WATER
GLYCERIN
1,2-HEXANEDIOL
BETA-GLUCAN
WATER
BUTYLENE GLYCOL
1,2-HEXANEDIOL
ULMUS DAVIDIANA ROOT EXTRACT
AMARANTHUS CAUDATUS SEED EXTRACT
GLYCERYL STEARATE
GLYCERIN
BUTYLENE GLYCOL
WATER
HYDROGENATED LECITHIN
FICUS CARICA (FIG) FRUIT EXTRACT
CENTELLA ASIATICA EXTRACT
1,2-HEXANEDIOL
CERAMIDE NP
SODIUM STEAROYL GLUTAMATE
ARGININE
CARBOMER
BETAINE
BEHENYL ALCOHOL
CETEARYL ALCOHOL
HYDROGENATED LECITHIN
GLYCERYL STEARATE SE
CHOLESTEROL
CERAMIDE NP
ETHYLHEXYLGLYCERIN
TOCOPHEROL
CARBOMER
WATER
1,2-HEXANEDIOL
GLYCOSAMINOGLYCANS
WATER
1,2-HEXANEDIOL
UNDARIA PINNATIFIDA EXTRACT
DISODIUM EDTA

PURPOSE

special skincare for dry and sensitive skin with abundant moisture and sea algae extract

keep out of reach of the children

INDICATIONS AND USAGE

apply proper amount to the skin

Keep out of reach of children.

Store in a cool, dry place and avoid direct sunlight.

Do not inhale or drink it.

Discontinue use if skin allergy or discomfort occurs.

DOSAGE AND ADMINISTRATION

for external use only